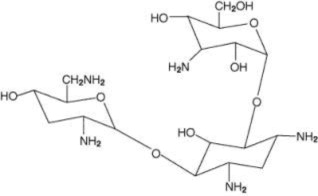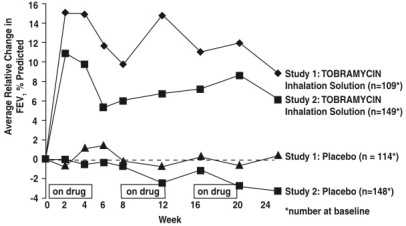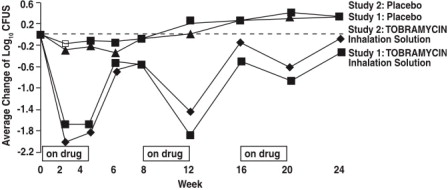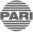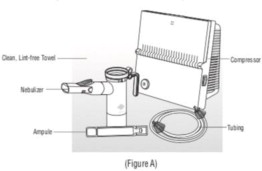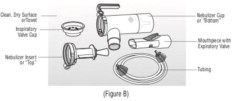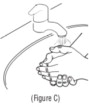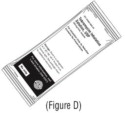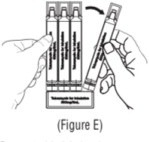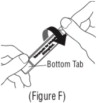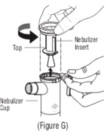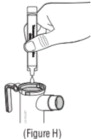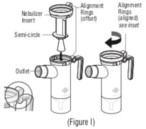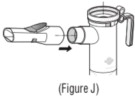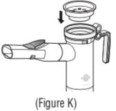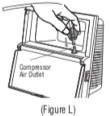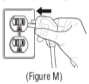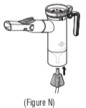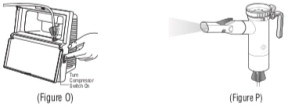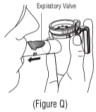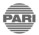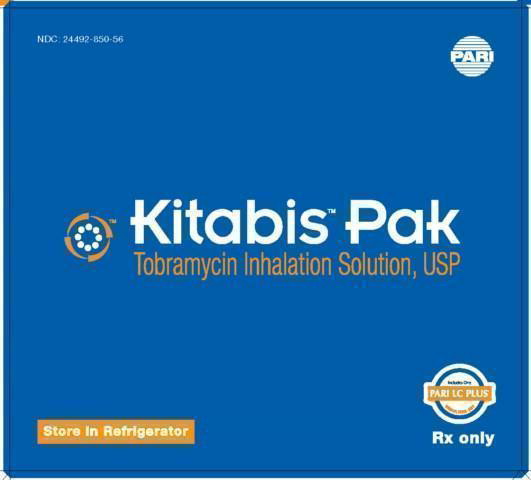 DRUG LABEL: Kitabis Pak
NDC: 24492-850 | Form: SOLUTION
Manufacturer: Pari Respiratory Equipment, Inc.
Category: prescription | Type: HUMAN PRESCRIPTION DRUG LABEL
Date: 20241122

ACTIVE INGREDIENTS: Tobramycin 300 mg/5 mL
INACTIVE INGREDIENTS: Sodium Chloride; Sulfuric Acid; Water

HIGHLIGHTS OF PRESCRIBING INFORMATION

These highlights do not include all the information needed to use KITABIS® PAK safely and effectively. See full prescribing information for KITABIS PAK.
KITABIS PAK (tobramycin inhalation solution), for oral inhalation use
Initial U.S. Approval: 1975

RECENT MAJOR CHANGES

Warnings and Precautions, Ototoxicity (5.2) | 03/2023

1 INDICATIONS AND USAGE

KITABIS PAK contains tobramycin, an aminoglycoside antibacterial drug indicated for the management of cystic fibrosis in adults and pediatric patients 6 years of age and older with Pseudomonas aeruginosa (1).

2 DOSAGE AND ADMINISTRATION

- KITABIS PAK is a co-packaging of tobramycin inhalation solution with a PARI LC PLUS® Reusable Nebulizer (2.1).
- Administer tobramycin inhalation solution as one single–use ampule (300 mg/5 mL) twice a day by oral inhalation in alternating periods of 28 days on drug, followed by 28 days off drug (2.1).
- Dosage is not adjusted by weight (2.1).
- Take doses as close to 12 hours apart as possible; but not less than 6 hours apart (2.1).
- Administer each 300 mg dose using the PARI LC PLUS Reusable Nebulizer and DeVilbiss® Pulmo-Aide® compressor (2.2).

3 DOSAGE FORMS AND STRENGTH

- Inhalation Solution: 300 mg in a single-use 5 mL ampule (3).

4 CONTRAINDICATIONS

- Known hypersensitivity to any aminoglycoside (4).

5 WARNINGS AND PRECAUTIONS

- Bronchospasm: Can occur with inhalation of tobramycin inhalation solution. Treat as medically appropriate, if it occurs (5.1).
- Ototoxicity: Tinnitus and hearing loss have been reported in patients receiving tobramycin inhalation solution. If noted, manage as medically appropriate, including potentially discontinuing tobramycin inhalation solution (5.2).
- Nephrotoxicity: Has been associated with aminoglycosides as a class. If nephrotoxicity develops, manage the patient as medically appropriate, including potentially discontinuing tobramycin inhalation solution (5.3).
- Neuromuscular Disorders: Aminoglycosides may aggravate muscle weakness because of a potential curare-like effect on neuromuscular function. If neuromuscular blockade occurs, it may be reversed by the administration of calcium salts but mechanical assistance may be necessary (5.4).
- Embryo-Fetal Toxicity: Aminoglycosides can cause fetal harm (5.5, 8.1)

6 ADVERSE REACTIONS

The most common adverse reactions (> 5%) in patients treated with tobramycin inhalation solution were increased cough, pharyngitis, increased sputum, dyspnea, hemoptysis, decreased lung function, voice alteration, taste perversion and rash (6.1).

To report SUSPECTED ADVERSE REACTIONS, contact PARI Respiratory Equipment at 1-844-548-2247 or FDA at 1-800-FDA-1088 or www.fda.gov/medwatch

7 DRUG INTERACTIONS

- Concurrent and/or sequential use with other drugs with neurotoxic, nephrotoxic or ototoxic potential should be avoided (7.1).
- Concomitant administration with ethacrynic acid, furosemide, urea, or intravenous mannitol is not recommended due to possible enhancement of aminoglycoside toxicity (7.2).

FULL PRESCRIBING INFORMATION

1 INDICATIONS AND USAGE

KITABIS PAK (co-packaging of tobramycin inhalation solution and PARI LC PLUS Reusable Nebulizer) is indicated for the management of cystic fibrosis in adults and pediatric patients 6 years of age and older with P. aeruginosa. Safety and efficacy have not been demonstrated in patients under the age of 6 years, patients with FEV1 < 25% or > 75% predicted, or patients colonized with Burkholderia cepacia [see Clinical Studies (14)].

2 DOSAGE AND ADMINISTRATION

2.1 Dosing Information

- KITABIS PAK is a co-packaging of tobramycin inhalation solution ampules with a PARI LC PLUS Reusable Nebulizer. Administer as follows: One single-use ampule (300 mg/5 mL) of tobramycin inhalation solution twice a day by oral inhalation in alternating periods of 28 days on drug, followed by 28 days off drug.
- The 300 mg/5 mL dose of tobramycin inhalation solution is the same for all patients regardless of age or weight.
- The doses should be taken as close to 12 hours apart as possible; they should not be taken less than 6 hours apart.

2.2 Administration of Tobramycin Inhalation Solution

Each dose of tobramycin inhalation solution is administered by oral inhalation using only the co-packaged PARI LC PLUS Reusable Nebulizer (Model No. 022B81-T) included in the KITABIS PAK, along with a DeVilbiss Pulmo-Aide air compressor (Model No. 5650D).

Tobramycin inhalation solution is not for subcutaneous, intravenous or intrathecal administration.

Prior to administration, read the Patient Information/Instructions for Use for KITABIS PAK for detailed information on how to use KITABIS PAK and follow the manufacturer's instructions for use and care of the DeVilbiss Pulmo-Aide air compressor.

The entire tobramycin inhalation solution treatment should take approximately 15 minutes to complete. Continue treatment until all the tobramycin inhalation solution has been delivered, and there is no longer any mist being produced.

Tobramycin inhalation solution should not be diluted or mixed with other drugs including dornase alfa in the nebulizer. Instruct patients on multiple therapies to take their medications prior to inhaling the tobramycin inhalation solution, or as directed by their physician.

Tobramycin inhalation solution should not be used if it is cloudy, if there are particles in the solution, or if it has been stored at room temperature for more than 28 days.

3 DOSAGE FORMS AND STRENGTH

Inhalation solution: 300 mg/5 mL in a single-use ampule

4 CONTRAINDICATIONS

Tobramycin inhalation solution is contraindicated in patients with a known hypersensitivity to any aminoglycoside.

5 WARNINGS AND PRECAUTIONS

5.1 Bronchospasm

Bronchospasm can occur with inhalation of tobramycin inhalation solution. In clinical studies with tobramycin inhalation solution, changes in FEV1 measured after the inhaled dose were similar in tobramycin inhalation solution and placebo groups. Bronchospasm that occurs during the use of tobramycin inhalation solution should be treated as medically appropriate.

5.2 Ototoxicity

Ototoxicity with use of Tobramycin Inhalation Solution

Transient tinnitus occurred in eight tobramycin inhalation solution treated patients versus no placebo patients in the clinical studies. Tinnitus may be a sentinel symptom of ototoxicity, and therefore the onset of this symptom warrants further clinical investigation. In postmarketing experience, patients receiving tobramycin inhalation solution have reported hearing loss. Ototoxicity, manifested as both auditory and vestibular toxicity, has been reported with parenteral aminoglycosides. Vestibular toxicity may be manifested by vertigo, ataxia or dizziness. Patients with known or suspected auditory or vestibular dysfunction should be closely monitored when taking tobramycin inhalation solution. Monitoring might include obtaining audiometric evaluations and serum tobramycin levels. If ototoxicity is noted, the patient should be managed as medically appropriate, including potentially discontinuing tobramycin inhalation solution [see Adverse Reactions (6.2)].

Risk of Ototoxicity Due to Mitochondrial DNA Variants

Cases of ototoxicity with aminoglycosides have been observed in patients with certain variants in the mitochondrially encoded 12S rRNA gene (MT-RNR1), particularly the m.1555A>G variant. Ototoxicity occurred in some patients even when their aminoglycoside serum levels were within the recommended range. Mitochondrial DNA variants are present in less than 1% of the general US population, and the proportion of the variant carriers who may develop ototoxicity as well as the severity of ototoxicity is unknown. In case of known maternal history of ototoxicity due to aminoglycoside use or a known mitochondrial DNA variant in the patient, consider alternative treatments other than aminoglycosides unless the increased risk of permanent hearing loss is outweighed by the severity of infection and lack of safe and effective alternative therapies.

5.3 Nephrotoxicity

Nephrotoxicity was not seen during clinical studies with tobramycin inhalation solution but has been associated with aminoglycosides as a class. Patients with known or suspected renal dysfunction or taking concomitant nephrotoxic drugs along with tobramycin inhalation solution should have serum concentrations of tobramycin and laboratory measurements of renal function obtained at the discretion of the treating physician. If nephrotoxicity develops, the patient should be managed as medically appropriate, including potentially discontinuing tobramycin inhalation solution.

5.4 Neuromuscular Disorders

Aminoglycosides, including tobramycin, may aggravate muscle weakness because of a potential curare-like effect on neuromuscular function. Neuromuscular blockade, respiratory failure, and prolonged respiratory paralysis may occur more commonly in patients with underlying neuromuscular disorders, such as myasthenia gravis or Parkinson's disease. Prolonged respiratory paralysis may also occur in patients receiving neuromuscular blocking agents. If neuromuscular blockade occurs, it may be reversed by the administration of calcium salts but mechanical assistance may be necessary.

5.5 Embryo-Fetal Toxicity

Aminoglycosides can cause fetal harm when administered to a pregnant woman. Aminoglycosides cross the placenta, and streptomycin has been associated with several reports of total, irreversible, bilateral congenital deafness in pediatric patients exposed in utero. However, systemic absorption of tobramycin following inhaled administration is expected to be minimal [see Clinical Pharmacology (12.3)]. Patients who use KITABIS PAK during pregnancy, or become pregnant while taking tobramycin inhalation solution should be apprised of the potential hazard to the fetus [see Use in Specific Populations (8.1)].

5.6 Concomitant Use of Systemic Aminoglycosides

Patients receiving concomitant tobramycin inhalation solution and parenteral aminoglycoside therapy should be monitored as clinically appropriate for toxicities associated with aminoglycosides as a class. Serum tobramycin levels should be monitored.

6 ADVERSE REACTIONS

The following serious adverse reactions are described below and elsewhere in the labeling:

- Bronchospasm [see Warnings and Precautions (5.1)]
- Ototoxicity [see Warnings and Precautions (5.2)]

6.1 Clinical Trials Experience

Because clinical trials are conducted under widely varying conditions, adverse reaction rates observed in the clinical trials of a drug cannot be directly compared to rates in the clinical trials of another drug and may not reflect the rates observed in practice.

Tobramycin inhalation solution was studied in two clinical studies in 258 cystic fibrosis patients ranging in age from 6 to 48 years. Patients received tobramycin inhalation solution in alternating periods of 28 days on and 28 days off drug in addition to their standard cystic fibrosis therapy for a total of 24 weeks. Adverse reactions reported in these studies are described below:

- The most frequent adverse reactions in the tobramycin inhalation arm were cough, pharyngitis, and increased sputum (see Table 1).
- Thirty-three patients (13%) treated with tobramycin inhalation solution complained of voice alteration compared to 17 (7%) placebo patients. Voice alteration was more common in the on-drug periods.
- Eight patients from the tobramycin inhalation solution group (3%) reported tinnitus compared to no placebo patients. All episodes were transient, resolved without discontinuation of the tobramycin inhalation solution treatment regimen, and were not associated with loss of hearing in audiograms.

Table 1 lists the percent of patients with selected adverse reactions that occurred in > 5% of tobramycin inhalation solution patients during the two Phase III studies.

Table 1: Percent of Patients with Selected Adverse Reactions Occurring in > 5% of Tobramycin Inhalation Solution Patients
Adverse Reaction | Tobramycin Inhalation Solution (n=258) % | Placebo (n=262) %
Cough Increased | 46.1 | 47.3
Pharyngitis | 38.0 | 39.3
Sputum Increased | 37.6 | 39.7
Dyspnea | 33.7 | 38.5
Hemoptysis | 19.4 | 23.7
Lung Function Decrease^1 | 16.3 | 15.3
Voice Alteration | 12.8 | 6.5
Taste Perversion | 6.6 | 6.9
Rash | 5.4 | 6.1
^1 Includes reported decreases in pulmonary function tests or decreased lung volume on chest radiograph associated with intercurrent illness or study drug administration.

Selected adverse reactions that occurred in less than or equal to 5% of patients treated with tobramycin inhalation solution:

Ear and labyrinth disorders

Tinnitus

Musculoskeletal and connective tissue disorders

Myalgia

Infections and infestations

Laryngitis

6.2 Postmarketing Experience

The following adverse reactions have been identified during post approval use of tobramycin inhalation solution. Because these reactions are reported voluntarily from a population of uncertain size, it is not always possible to reliably estimate their frequency or establish a causal relationship to drug exposure.

Ear and labyrinth disorders

Hearing loss: Some of these reports occurred in patients with previous or concomitant treatment with systemic aminoglycosides. Patients with hearing loss frequently reported tinnitus. [see Warnings and Precautions (5.2)]

Skin and subcutaneous tissue disorders

Hypersensitivity, pruritus, urticaria, rash

Nervous system disorders

Aphonia, dysgeusia

Respiratory, thoracic, and mediastinal disorders

Bronchospasm [see Warnings and Precautions (5.1)], oropharyngeal pain

7 DRUG INTERACTIONS

7.1 Drugs with Neurotoxic, Nephrotoxic or Ototoxic Potential

Concurrent and/or sequential use of tobramycin inhalation solution with other drugs with neurotoxic, nephrotoxic, or ototoxic potential should be avoided if possible.

7.2 Diuretics

Some diuretics can enhance aminoglycoside toxicity by altering aminoglycoside concentrations in serum and tissue. Tobramycin inhalation solution should not be administered concomitantly with ethacrynic acid, furosemide, urea, or intravenous mannitol.

8 USE IN SPECIFIC POPULATIONS

8.1 Pregnancy

Risk Summary

Aminoglycosides can cause fetal harm. Published literature reports that use of streptomycin, an aminoglycoside, can cause total, irreversible, bilateral congenital deafness when administered to a pregnant woman [Warnings and Precautions (5.5)]. Although there are no available data on KITABIS PAK use in pregnant women to inform a drug-associated risk of major birth defects, miscarriage, or adverse maternal or fetal outcomes, systemic absorption of tobramycin following inhaled administration is expected to be minimal [see Clinical Pharmacology (12.3)]. There are risks to the mother associated with cystic fibrosis in pregnancy (see Clinical Considerations).

In animal reproduction studies with subcutaneous administration of tobramycin in pregnant rats and rabbits during organogenesis there were no adverse developmental outcomes; however, ototoxicity was not evaluated in the offspring from these studies (see Data). Advise pregnant women of the potential risk to a fetus.

The estimated background risk of major birth defects and miscarriage for the indicated populations are unknown. All pregnancies have a background risk of birth defect, loss, or other adverse outcomes. In the U.S. general population, the estimated background risk of major birth defects and miscarriage in clinically recognized pregnancies is 2 to 4% and 15 to 20%, respectively.

Clinical Considerations

Disease-Associated Maternal and/or Embryo/Fetal Risk

Cystic fibrosis may increase the risk for preterm delivery.

Data

Animal Data

No reproductive toxicity studies have been conducted with tobramycin inhalation solution. However, subcutaneous administration of tobramycin at doses of up to 100 (rat) or 20 (rabbit) mg/kg/day during organogenesis was not associated with adverse developmental outcomes. Subcutaneous doses of tobramycin ≥40 mg/kg/day were severely maternally toxic to rabbits and precluded the evaluation of adverse developmental outcomes. Ototoxicity was not evaluated in offspring during non-clinical reproductive toxicity studies with tobramycin.

8.2 Lactation

Risk Summary

There are no data on the presence of tobramycin inhalation solution in either human or animal milk, the effects on the breastfed infant, or the effects on milk production. Limited published data on other formulations of tobramycin in lactating women indicate that tobramycin is present in human milk. However, systemic absorption of tobramycin following inhaled administration is expected to be minimal [see Clinical Pharmacology (12.3)]. Tobramycin may cause alteration in the intestinal flora of the breastfeeding infant (see Clinical Considerations). The developmental and health benefits of breastfeeding should be considered along with the mother's clinical need for KITABIS PAK and any potential adverse effects on the breastfed infant from KITABIS PAK or from the underlying maternal condition.

Clinical Considerations

Tobramycin may cause intestinal flora alteration. Advise a woman to monitor the breastfed infant for loose or bloody stools and candidiasis (thrush, diaper rash).

8.4 Pediatric Use

The safety and efficacy of tobramycin inhalation solution have not been studied in pediatric patients under 6 years of age.

8.5 Geriatric Use

Clinical studies of tobramycin inhalation solution did not include patients aged 65 years and over. Tobramycin is known to be substantially excreted by the kidney, and the risk of adverse reactions to this drug may be greater in patients with impaired renal function. Because elderly patients are more likely to have decreased renal function, it may be useful to monitor renal function [see Warnings and Precautions (5.3)].

10 OVERDOSAGE

Signs and symptoms of acute toxicity from overdosage of IV tobramycin might include dizziness, tinnitus, vertigo, loss of high-tone hearing acuity, respiratory failure, and neuromuscular blockade. Administration by inhalation results in low systemic bioavailability of tobramycin. Tobramycin is not significantly absorbed following oral administration. Tobramycin serum concentrations may be helpful in monitoring overdosage.

11 DESCRIPTION

KITABIS PAK contains tobramycin inhalation solution, USP and the PARI LC PLUS Reusable Nebulizer (PARI LC PLUS). Tobramycin inhalation solution is a sterile, clear, slightly yellow, non-pyrogenic, aqueous solution with the pH and salinity adjusted specifically for administration by a compressed air driven PARI LC PLUS Reusable Nebulizer. The chemical formula for tobramycin is C18H37N5O9 and the molecular weight is 467.52. Tobramycin is O-3-amino-3-deoxy-α-D-glucopyranosyl-(1→4)-O-[2,6-diamino-2,3,6-trideoxy-a-D-ribo - hexopyranosyl-(1→6)]-2-deoxy-L-streptamine. The structural formula for tobramycin is:

Each single-use 5 mL ampule contains 300 mg tobramycin and 11.25 mg sodium chloride in sterile water for injection. Sulfuric acid and sodium hydroxide are added to adjust the pH to 6.0. Nitrogen is used for sparging. The formulation contains no preservatives. The inhalation solution has an osmolality in the range 135 to 200 mOsmol/kg.

The PARI LC PLUS Reusable Nebulizer has the following performance characteristics with tobramycin inhalation solution [measured using Next Generation Impactor (NGI) at 15 L/min continuous flow, standard conditions (50%RH, 23°C)]: (1) Delivered Dose: 174 mg; (2) Fine Particle Dose (< 5μm): 97 mg; (3) Nebulization Time: 13 min.; (4) Mass Median Aerodynamic Diameter: 4.3 μm; (5) Geometric Standard Deviation (GSD): 2.2 μm.

12 CLINICAL PHARMACOLOGY

12.1 Mechanism of Action

Tobramycin is an aminoglycoside antibacterial [see Microbiology (12.4)].

12.3 Pharmacokinetics

Absorption

Tobramycin inhalation solution contains tobramycin, a cationic polar molecule that does not readily cross epithelial membranes.^1 The bioavailability of tobramycin inhalation solution may vary because of individual differences in nebulizer performance and airway pathology.^2 Following administration of tobramycin inhalation solution, tobramycin remains concentrated primarily in the airways.

Sputum Concentrations

Ten minutes after inhalation of the first 300 mg dose of tobramycin inhalation solution, the average concentration of tobramycin was 1237 mcg/g (ranging from 35 to 7414 mcg/g) in sputum. Tobramycin does not accumulate in sputum; after 20 weeks of therapy with the tobramycin inhalation solution regimen, the average concentration of tobramycin at ten minutes after inhalation was 1154 mcg/g (ranging from 39 to 8085 mcg/g) in sputum. High variability of tobramycin concentration in sputum was observed. Two hours after inhalation, sputum concentrations declined to approximately 14% of tobramycin levels at ten minutes after inhalation.

Serum Concentrations

The average serum concentration of tobramycin one hour after inhalation of a single 300 mg dose of tobramycin inhalation solution by cystic fibrosis patients was 0.95 mcg/mL. After 20 weeks of therapy on the tobramycin inhalation solution regimen, the average serum tobramycin concentration one hour after dosing was 1.05 mcg/mL.

Distribution

Following administration of tobramycin inhalation solution, tobramycin remains concentrated primarily in the airways. Binding of tobramycin to serum proteins is negligible.

Elimination

Metabolism

Tobramycin is not metabolized.

Excretion

The elimination half-life of tobramycin from serum is approximately 2 hours after intravenous (IV) administration. Assuming tobramycin absorbed following inhalation behaves similarly to tobramycin following IV administration, systemically absorbed tobramycin is eliminated principally by glomerular filtration. Unabsorbed tobramycin, following tobramycin inhalation solution administration, is likely eliminated primarily in expectorated sputum.

12.4 Microbiology

Mechanism of Action

Tobramycin is an aminoglycoside antibacterial produced by Streptomyces tenebrarius. It acts primarily by disrupting protein synthesis, leading to altered cell membrane permeability, progressive disruption of the cell envelope, and eventual cell death.^3

Tobramycin has in vitro activity against Gram-negative bacteria including P. aeruginosa. It is bactericidal in vitro at peak concentrations equal to or slightly greater than the minimum inhibitory concentration.

Resistance

Treatment for 6 months with tobramycin inhalation solution in two clinical studies did not affect the susceptibility of the majority of P. aeruginosa isolates tested; however, increased minimum inhibitory concentrations (MICs) were noted in some patients. The clinical significance of this information has not been clearly established in the treatment of P. aeruginosa in cystic fibrosis patients [see Clinical Studies (14)].

Susceptibility Testing

Interpretive criteria for inhaled antibacterial products are not defined. The in vitro antimicrobial susceptibility test methods used for parenteral tobramycin therapy can be used to monitor the susceptibility of P. aeruginosa isolated from cystic fibrosis patients.^4,5,6 If decreased susceptibility is noted, the results should be reported to the clinician. Susceptibility breakpoints established for parenteral administration of tobramycin do not apply to aerosolized administration of tobramycin inhalation solution. The relationship between in vitro susceptibility test results and clinical outcome with tobramycin inhalation solution therapy is not clear. A single sputum sample from a cystic fibrosis patient may contain multiple morphotypes of Pseudomonas aeruginosa and each morphotype may have a different level of in vitro susceptibility to tobramycin.

For specific information regarding susceptibility test interpretive criteria and associated test methods and quality control standards recognized by FDA for this drug, please see: https://www.fda.gov/STIC.

13 NONCLINICAL TOXICOLOGY

13.1 Carcinogenesis, Mutagenesis, Impairment of Fertility

A two-year rat inhalation toxicology study to assess carcinogenic potential of tobramycin inhalation solution has been completed. Rats were exposed to tobramycin inhalation solution for up to 1.5 hours per day for 95 weeks. The clinical formulation of the drug was used for this carcinogenicity study. Serum levels of tobramycin of up to 35 mcg/mL were measured in rats, in contrast to the average 1 mcg/mL levels observed in cystic fibrosis patients in clinical trials. There was no drug-related increase in the incidence of any variety of tumor.

Additionally, tobramycin has been evaluated for genotoxicity in a battery of in vitro and in vivo tests. The Ames bacterial reversion test, conducted with 5 tester strains, failed to show a significant increase in revertants with or without metabolic activation in all strains. Tobramycin was negative in the mouse lymphoma forward mutation assay, did not induce chromosomal aberrations in Chinese hamster ovary cells, and was negative in the mouse micronucleus test.

Subcutaneous administration of up to 100 mg/kg of tobramycin did not affect mating behavior or cause impairment of fertility in male or female rats.

14 CLINICAL STUDIES

Two identically designed, double-blind, randomized, placebo-controlled, parallel group, 24-week clinical studies (Study 1 and Study 2) at a total of 69 cystic fibrosis centers in the United States were conducted in cystic fibrosis patients with P. aeruginosa with tobramycin inhalation solution. Subjects who were less than 6 years of age, had a baseline creatinine of > 2 mg/dL, or had B. cepacia isolated from sputum were excluded. All subjects had baseline FEV1% predicted between 25% and 75%. In these clinical studies, 258 patients received tobramycin inhalation solution therapy on an outpatient basis (see Table 2) using a PARI LC PLUS nebulizer along with a DeVilbiss Pulmo-Aide compressor.

Table 2: Dosing Regimens in Clinical Studies
 | Cycle 1 |  | Cycle 2 |  | Cycle 3
 | 28 days | 28 days | 28 days | 28 days | 28 days | 28 days
TOBRAMYCIN Inhalation Solution regimen n=258 | TOBRAMYCIN Inhalation Solution 300 mg twice daily | No drug | TOBRAMYCIN Inhalation Solution 300 mg twice daily | No drug | TOBRAMYCIN Inhalation Solution 300 mg twice daily | No drug
Placebo regimen n=262 | Placebo twice daily |  | Placebo twice daily |  | Placebo twice daily

All patients received either tobramycin inhalation solution or placebo (saline with 1.25 mg quinine for flavoring) in addition to standard treatment recommended for cystic fibrosis patients, which included oral and parenteral anti-pseudomonal therapy, Beta 2-agonists, cromolyn, inhaled steroids, and airway clearance techniques. In addition, approximately 77% of patients were concurrently treated with dornase alfa.

In each study, tobramycin inhalation solution-treated patients experienced significant improvement in pulmonary function. Improvement was demonstrated in the tobramycin inhalation solution group in Study 1 by an average increase in FEV1% predicted of about 11% relative to baseline (Week 0) during 24 weeks compared to no average change in placebo patients. In Study 2, tobramycin inhalation solution-treated patients had an average increase of about 7% compared to an average decrease of about 1% in placebo patients. Figure 1 shows the average relative change in FEV1% predicted over 24 weeks for both studies.

Figure 1: Relative Change From Baseline in FEV1% Predicted

In each study, tobramycin inhalation solution therapy resulted in a significant reduction in the number of P. aeruginosa colony forming units (CFUs) in sputum during the on-drug periods. Sputum bacterial density returned to baseline during the off-drug periods. Reductions in sputum bacterial density were smaller in each successive cycle. (see Figure 2).

Figure 2: Absolute Change From Baseline in Log10 CFUs

Patients treated with tobramycin inhalation solution were hospitalized for an average of 5.1 days compared to 8.1 days for placebo patients. Patients treated with tobramycin inhalation solution required an average of 9.6 days of parenteral anti-pseudomonal antibiotic treatment compared to 14.1 days for placebo patients. During the 6 months of treatment, 40% of tobramycin inhalation solution patients and 53% of placebo patients were treated with parenteral anti-pseudomonal antibiotics.

The relationship between in vitro susceptibility test results and clinical outcome with tobramycin inhalation solution therapy is not clear. However, 4 tobramycin inhalation solution patients who began the clinical trial with P. aeruginosa isolates having MIC values ≥ 128 μg/mL did not experience an improvement in FEV1 or a decrease in sputum bacterial density.

15 REFERENCES

1. Neu HC. Tobramycin: an overview. [Review]. J Infect Dis 1976; Suppl 134:S3-19.
2. Weber A, Smith A, Williams-Warren J et al. Nebulizer delivery of tobramycin to the lower respiratory tract. Pediatr Pulmonol 1994; 17 (5):331-9.
3. Bryan LE. Aminoglycoside resistance. Bryan LE, Ed. Antimicrobial drug resistance. Orlando, FL: Academic Press, 1984: 241-77.
4. Clinical and Laboratory Standards Institute (CLSI). Methods for Dilution Antimicrobial Susceptibility Tests for Bacteria that Grow Aerobically; Approved Standard - Ninth Edition. CLSI document M07-A9, Clinical and Laboratory Standards Institute, 950 West Valley Road, Suite 2500, Wayne, Pennsylvania 19087, USA, 2012.
5. Clinical and Laboratory Standards Institute (CLSI). Performance Standards for Antimicrobial Disk Diffusion Susceptibility Tests; Approved Standard – Eleventh Edition. CLSI document M02-A11, Clinical and Laboratory Standards Institute, 950 West Valley Road, Suite 2500, Wayne, Pennsylvania 19087, USA, 2012.
6. Clinical and Laboratory Standards Institute (CLSI). Performance Standards for Antimicrobial Susceptibility Testing; Twenty-fourth Informational Supplement, CLSI document M100-S24, Clinical and Laboratory Standards Institute, 950 West Valley Road, Suite 2500, Wayne, Pennsylvania 19087, USA, 2014.

16 HOW SUPPLIED / STORAGE AND HANDLING

16.1 How Supplied

KITABIS PAK co-packaged kit (NDC 24492-850-56) is available in cartons containing one reusable PARI LC PLUS nebulizer (Model No.: 022B81-T) and 14 tobramycin inhalation solution pouches. Each pouch contains four 300 mg/5 ml ampules of tobramycin inhalation solution for a total of 56 ampules in each carton. Each carton constitutes a 28 day supply.

16.2 Storage

- Tobramycin inhalation solution should be stored under refrigeration at 2-8°C/36-46°F. Upon removal from the refrigerator, or if refrigeration is unavailable, tobramycin inhalation solution pouches (opened or unopened) may be stored at room temperature (up to 25°C/77°F) for up to 28 days. Tobramycin inhalation solution should not be used beyond the expiration date stamped on the ampule when stored under refrigeration (2-8°C/36-46°F) or beyond 28 days when stored at room temperature (25°C/77°F).
- Tobramycin inhalation solution ampules should not be exposed to intense light. The solution in the ampule is slightly yellow, but may darken with age if not stored in the refrigerator; however, the color change does not indicate any change in the quality of the product as long as it is stored within the recommended storage conditions.

17 PATIENT COUNSELING INFORMATION

Advise the patient to read the FDA-approved patient labeling (Patient Information and Instructions for Use).

Instructions for Administration

Instruct patients to read the Instructions for Use before starting KITABIS PAK. Instruct patients to use the tobramycin inhalation solution in KITABIS PAK only with the PARI LC PLUS Reusable Nebulizer included in the KITABIS PAK.

Difficulty Breathing

Advise patients to inform their physicians if they experience shortness of breath or wheezing after administration of tobramycin inhalation solution. Tobramycin inhalation solution can cause a narrowing of the airway [see Warnings and Precautions (5.1)].

Hearing Loss

Advise patients to inform their physician if they experience ringing in the ears, dizziness, or any changes in hearing because tobramycin inhalation solution has been associated with hearing loss [see Warnings and Precautions (5.2)].

Kidney Damage

Advise patients to inform their physician if they have any history of kidney problems because tobramycin inhalation solution is in a class of drugs that have caused kidney damage [see Warnings and Precautions (5.3)].

Embryo-Fetal Toxicity:

Advise pregnant women that aminoglycosides can cause irreversible congenital deafness when administered to a pregnant woman [see Warnings and Precautions (5.5) and Use in Specific Populations (8.1)].

Lactation:

Advise a woman to monitor their breastfed infants for diarrhea and/or bloody stools [see Use in Specific Populations (8.2)].

Additional Information

PARI LC PLUS® Reusable Nebulizer: 1-800-327-8632

DeVilbiss® Pulmo-Aide® Air Compressor: 1-800-338-1988

KITABIS PAK: 1-844-KITABIS (548-2247)

Manufactured by:

Woodstock Sterile Solutions, Inc.Woodstock, IL 60098

Distributed by:

PARI Respiratory Equipment, Inc.

2412 PARI Way, Midlothian, VA 23112

850D5601 Rev. F 08/2023 v5

©2023 PulmoFlow, Inc. All rights reserved.

PATIENT INFORMATION
KITABIS® PAK (Ki TAH biss Pak)
(tobramycin inhalation solution) for oral inhalation

Read this Patient Information before you start using KITABIS PAK and each time you get a refill. There may be new information. This information does not take the place of talking with your healthcare provider about your medical condition or your treatment.

What is KITABIS PAK?
KITABIS PAK contains a prescription medicine and a PARI LC PLUS Reusable Nebulizer used to treat adults and children 6 years of age and older with cystic fibrosis who have a bacterial infection called Pseudomonas aeruginosa.

KITABIS PAK contains an antibacterial medicine called tobramycin (an aminoglycoside).
It is not known if tobramycin inhalation solution is safe and effective:

- in children under 6 years of age.
- in people who have an FEV1 less than 25% or greater than 75% predicted.
- in people who are colonized with a bacterium called Burkholderia cepacia.
- when used for more than 3 cycles.

Who should not use KITABIS PAK?
Do not use KITABIS PAK if you are allergic to tobramycin, any of the ingredients in KITABIS PAK, or to any other aminoglycoside antibacterial medicine.

What should I tell my healthcare provider before using KITABIS PAK?
Before using KITABIS PAK, tell your healthcare provider about all of your medical conditions, including if you:

- have or have had breathing problems such as wheezing, coughing, or chest tightness.
- have or have had hearing problems (including noises in your ears such as ringing or hissing), hearing loss, or your mother has had hearing problems after taking an aminoglycoside.
- have been told you have certain gene variants (a change in the gene) related to hearing abnormalities inherited from your mother.
- have dizziness.
- have or have had kidney problems.
- have or have had problems with muscle weakness such as myasthenia gravis or Parkinson's disease.
- are pregnant or plan to become pregnant. KITABIS PAK contains a medicine that may cause harm to your unborn baby. See “What are the possible side effects of KITABIS PAK?” below for more information.
- are breastfeeding or plan to breastfeed. It is not known if the medicine in KITABIS PAK (tobramycin inhalation solution) passes into your breast milk.

Tell your healthcare provider about all the medicines you take, including prescription and over-the-counter, vitamins, and herbal supplements.
Using KITABIS PAK with certain other medicines can cause serious side effects. Ask your healthcare provider or pharmacist for a list of these medicines, if you are not sure. Know the medicines you take. Keep a list of them and show it to your healthcare provider and pharmacist when you get a new medicine.
If you are using KITABIS PAK, you should discuss with your healthcare provider if you should take:

- other medicines that may harm your nervous system, kidneys, or hearing
- “water pills” (diuretics) such as Edecrin (ethacrynic acid), Lasix (furosemide), or mannitol
- urea

How should I use KITABIS PAK?

- See the step-by-step Instructions for Use at the end of this Patient Information leaflet about the right way to use KITABIS PAK.
- Use KITABIS PAK exactly as your healthcare provider tells you to. Ask your healthcare provider or pharmacist if you are not sure.
- The usual dose of KITABIS PAK for adults and children 6 years of age and over is:
  - 1 ampule of tobramycin inhalation solution inhaled by mouth in the morning and 1 ampule of tobramycin inhalation solution inhaled by mouth in the evening using your PARI LC PLUS Reusable Nebulizer with a DeVilbiss® Pulmo-Aide air compressor.
- Each dose of KITABIS PAK should take about 15 minutes to finish.
- Each dose of KITABIS PAK should be used as close to 12 hours apart as possible.
- Do not use your dose of KITABIS PAK less than 6 hours apart.
- After using KITABIS PAK for 28 days, you should stop using it for 28 days. After you have stopped using KITABIS PAK for 28 days, you should start using KITABIS PAK again for 28 days. It is important that you keep to the 28-day on, 28-day off cycle.
- Do not mix the medicine in KITABIS PAK with other medicines including dornase alfa in your nebulizer.
- If you are taking other medicines inhaled through your mouth (bronchodilators), your healthcare provider will tell you how to take your medicine the right way.
- If you inhale too much of the medicine in KITABIS PAK, tell your healthcare provider right away.

What are the possible side effects of KITABIS PAK?
KITABIS PAK can cause serious side effects, including:

- severe breathing problems (bronchospasm).Tell your healthcare provider right away if you get any of these symptoms of bronchospasm while using KITABIS PAK:
  - shortness of breath with wheezing
  - coughing and chest tightness
- hearing loss or ringing in the ears (ototoxicity). Tell your healthcare provider right away if you have hearing loss or hear noises in your ears (such as ringing or hissing), or if you develop vertigo, dizziness, or difficulty with balance.
- worsening kidney problems (nephrotoxicity). Your healthcare provider may do a blood test and urine test to check how your kidneys are working while you are using KITABIS PAK.
- worsening muscle weakness. The medicine in KITABIS PAK (tobramycin inhalation solution) is in a class of medicines that can cause muscle weakness to get worse in people who already have problems with muscle weakness (myasthenia gravis or Parkinson's disease).
- The medicine in KITABIS PAK (tobramycin inhalation solution) is in a class of medicines which may cause harm to an unborn baby.

The most common side effects of KITABIS PAK include:

- cough
- sore throat
- productive cough

- shortness of breath
- coughing up blood
- worsening of lung problems or cystic fibrosis

- changes in your voice (hoarseness)
- altered taste
- rash

These are not all of the possible side effects of KITABIS PAK. Call your doctor for medical advice about side effects. You may report side effects to FDA at 1-800-FDA-1088.

General information about the safe and effective use of KITABIS PAK.
Medicines are sometimes prescribed for purposes other than those listed in a patient information leaflet. Do not use KITABIS PAK for a condition for which it was not prescribed. Do not give KITABIS PAK to other people, even if they have the same symptoms that you have. It may harm them.
You can ask your healthcare provider or pharmacist for information about KITABIS PAK that is written for health professionals.

What are the ingredients in KITABIS PAK?
Active ingredient: tobramycin
Inactive ingredients: sodium chloride in sterile water, sulfuric acid, and sodium hydroxide (for pH adjustment)

INSTRUCTIONS FOR USE

KITABIS PAK (Ki TAH biss Pak)

(tobramycin inhalation solution), for oral inhalation

Follow the instructions below for using KITABIS PAK which contains tobramycin inhalation solution and the PARI LC PLUS Reusable Nebulizer (PARI LC PLUS). If you have any questions, ask your healthcare provider or pharmacist.

Each KITABIS PAK carton (28-day supply) contains 56 tobramycin inhalation solution ampules packed in 14 foil pouches that each contain 4 single use tobramycin inhalation solution ampules.

You will need the following supplies (See Figure A):

- 1 tobramycin inhalation solution ampule
- PARI LC PLUS Reusable Nebulizer
- DeVilbiss Pulmo-Aide (Pulmo-Aide) air compressor
- tubing to connect the nebulizer and compressor
- clean, lint-free towel
- nose clip (optional, not pictured)

Note: Read the Instructions for Use that come with your PARI LC PLUS Reusable Nebulizer and DeVilbiss Pulmo-Aide air compressor for detailed instructions on how to use and care for your nebulizer and air compressor before you use it.

Do not mix the medicine in KITABIS PAK with other medicines in your nebulizer.

The medicine in KITABIS PAK (tobramycin inhalation solution) comes in a sealed foil pouch. Do not open a sealed pouch until you are ready to use a dose. After opening the pouch, unopened ampules should be returned to and stored in the pouch.

Getting ready:

- Open the PARI LC PLUS package. Place the PARI LC PLUS parts including Top and Bottom (Nebulizer Cup) Assembly, Inspiratory Valve Cap, Mouthpiece with Valve, and Tubing on a clean, dry surface or towel (See Figure B).

Preparing your KITABIS PAK dose:

Step 1: Wash your hands with soap and water (See Figure C).

Step 2: Open the foil pouch (See Figure D).

Step 3: Separate 1 ampule by gently pulling apart starting at the top of the ampules and continue down to the bottom tabs (See Figure E) and use it right away.

Step 4: Hold the bottom tab on the KITABIS PAK ampule with 1 hand (See Figure F). With your other hand, hold the top of the ampule and twist off the top of the ampule (See Figure F).

- Do not squeeze the ampule until you are ready to squeeze all of the medicine into the Nebulizer Cup.

Step 5: Hold the Nebulizer Cup and twist off the Nebulizer Insert or Top in a counter-clockwise direction (See Figure G). Set the Top aside on a clean, dry, surface.

Step 6: Squeeze all the medicine from the ampule into the Nebulizer Cup (See Figure H).

Step 7: Replace the Nebulizer Insert. Line up the semicircle on the Nebulizer Insert with the Nebulizer Outlet and twist on the Nebulizer Insert in a clockwise direction until it is tight and the alignment rings are lined up (See Figure I).

Step 8: Push the Mouthpiece straight onto the Nebulizer Cup (See Figure J).

Step 9: Firmly push the Inspiratory Valve Cap straight down onto the Nebulizer Cup Top (See Figure K). The Inspiratory Valve Cap should fit tightly.

Step 10: Connect 1 end of the tubing to the compressor air outlet (See Figure L). The tubing should fit tightly.

Step 11: Plug your compressor into an electrical outlet (See Figure M).

Step 12: Hold the Nebulizer Cup upright and firmly push the free end of the tubing straight up onto the Air Intake on the bottom of the Nebulizer Cup (See Figure N). Make sure to keep the Nebulizer Cup upright.

Giving your KITABIS PAK dose:

Step 13: Turn on the compressor (See Figure O). You should see a steady mist coming from the Mouthpiece (See Figure P).

Step 14: Sit or stand in a comfortable, upright position that will allow you to breathe normally. Place the Mouthpiece between your teeth and on top of your tongue and breathe normally only through your mouth (See Figure Q).

- Nose clips may help you breathe only through your mouth and not through your nose.

Step 15: Keep breathing in your KITABIS PAK dose for at least 15 minutes. You will know that you have received your full dose of medicine when you hear a “sputtering noise” coming from the Mouthpiece for at least 1 minute and the Nebulizer Cup is empty.

After your KITABIS PAK dose:

Step 16: Clean and disinfect your nebulizer (see manufacturer's Instructions for Use).

Care and Use of your DeVilbiss Pulmo-Aide compressor:

Follow the manufacturer's instructions for care and use of your compressor.

How should I store KITABIS PAK?

- Store tobramycin inhalation solution in the refrigerator between 36°F to 46°F (2°C to 8°C) until needed.
- You may store the tobramycin inhalation solution in the foil pouches (opened or unopened) at room temperature between 68°F to 77°F (20°C to 25°C) for up to 28 days.
- Do not use tobramycin inhalation solution after the expiration date stamped on the ampule.
- Keep tobramycin inhalation solution in the foil pouch and out of the light.
- Tobramycin inhalation solution is normally slightly yellow, but may get darker with age if unrefrigerated. The color change does not change how the medicine works.
- Do not use tobramycin inhalation solution if it is cloudy, has particles in the solution, or if it has been stored at room temperature for more than 28 days. Throw the applicable ampule(s) away in your household trash and get a new ampule.

Keep KITABIS PAK and all medicines out of the reach of children.

This Patient Information and Instructions for Use have been approved by the U.S. Food and Drug Administration.

Revised: 08/2023

Additional InformationPARI LC PLUS® Reusable Nebulizer: 1-800-327-8632
DeVilbiss® Pulmo-Aide® Air Compressor: 1-800-338-1988 KITABIS PAK: 1-844-KITABIS (548-2247)

Manufactured by:
Woodstock Sterile Solutions, Inc.
Woodstock, IL 60098

Distributed by:

PARI Respiratory Equipment, Inc.
2412 PARI Way, Midlothian, VA 23112

850D5601 Rev. F 08/23 v5

©2023 PulmoFlow, Inc. All rights reserved.

Principal Display Panel - Kitabis Pak

NDC: 24492-850-56

PARI

KitabisTM Pak

Tobramycin Inhalation Solution, USP

Store in Refrigerator

Includes One PARI LC PLUS Nebulizer Set

Rx only